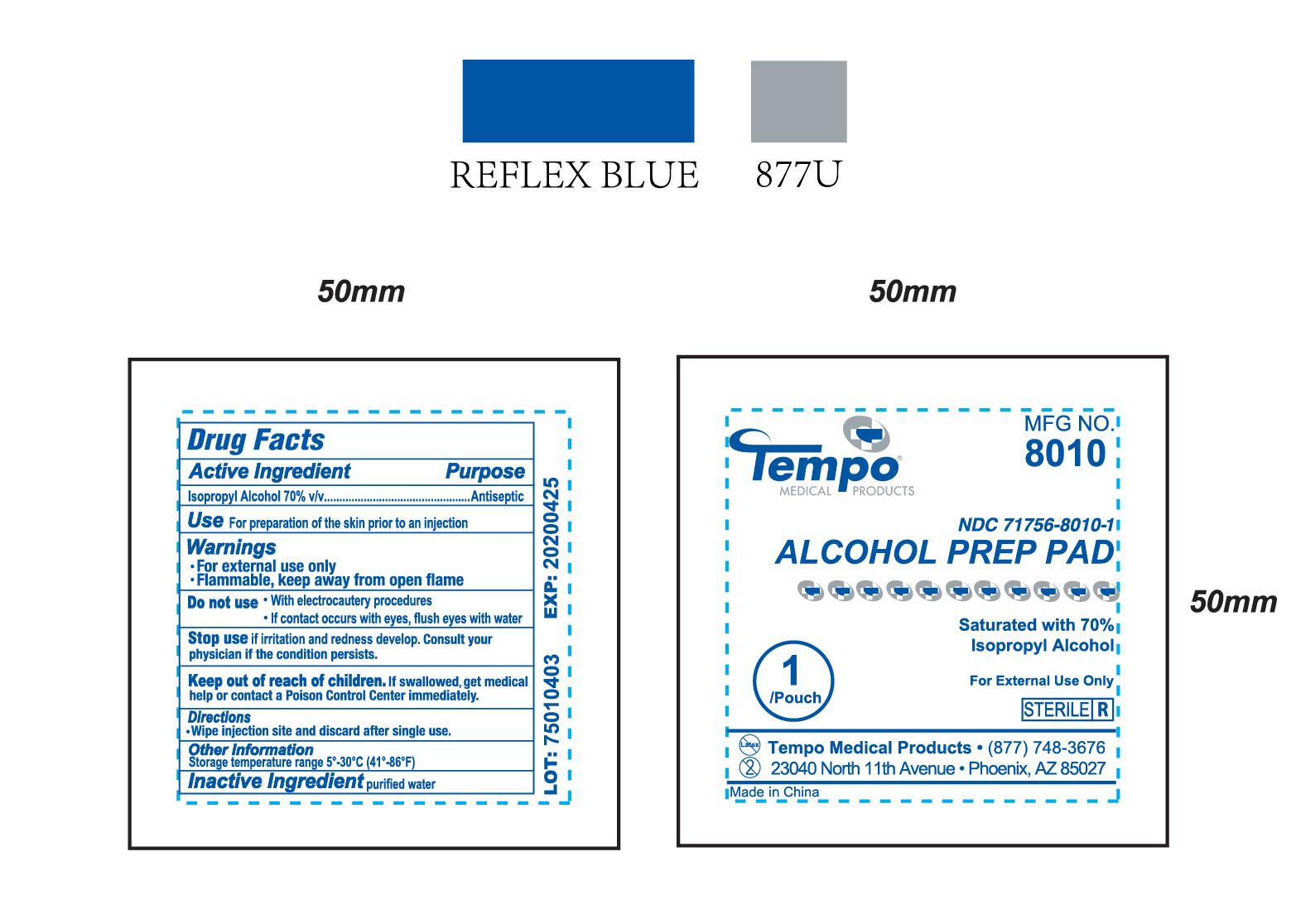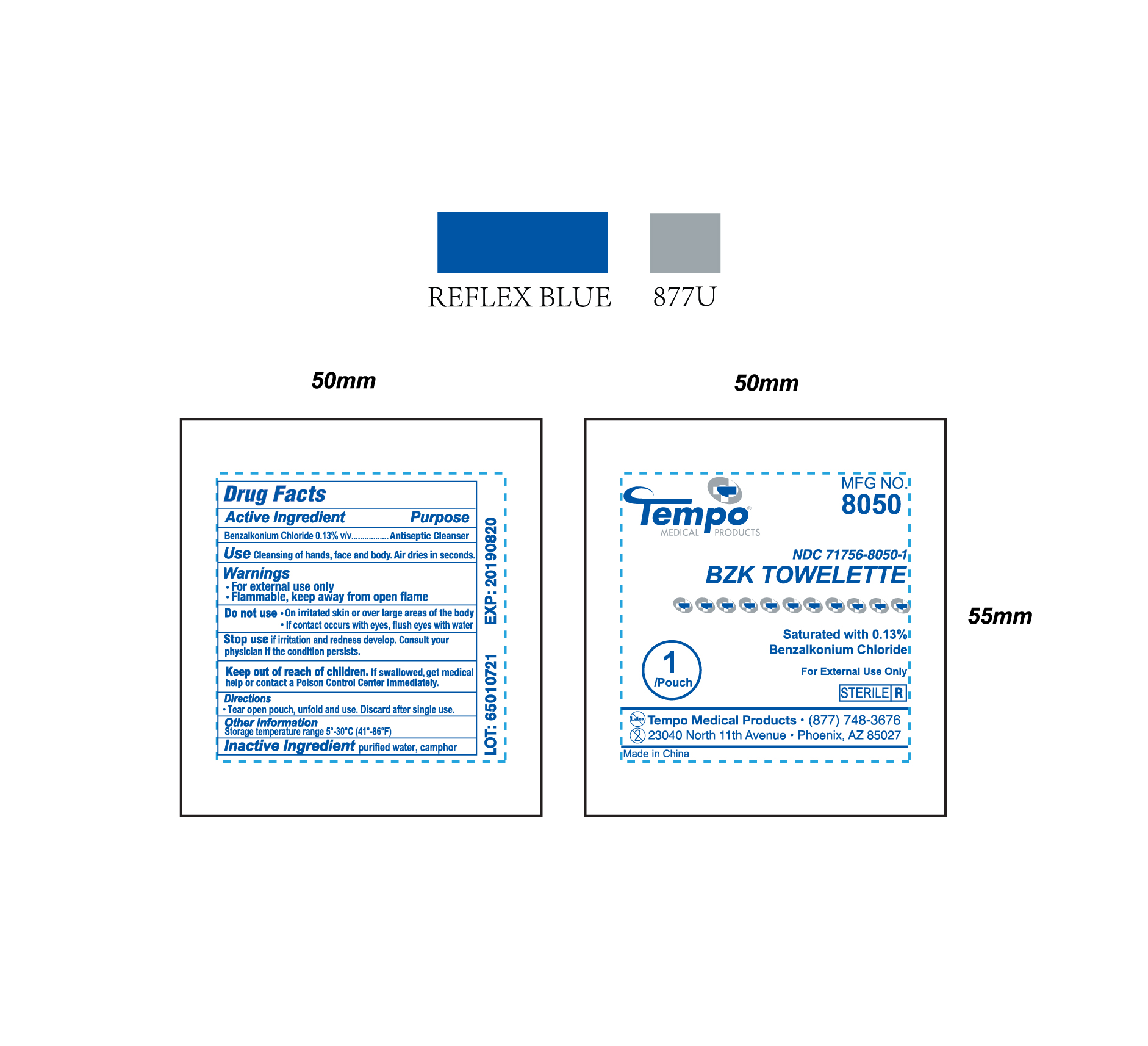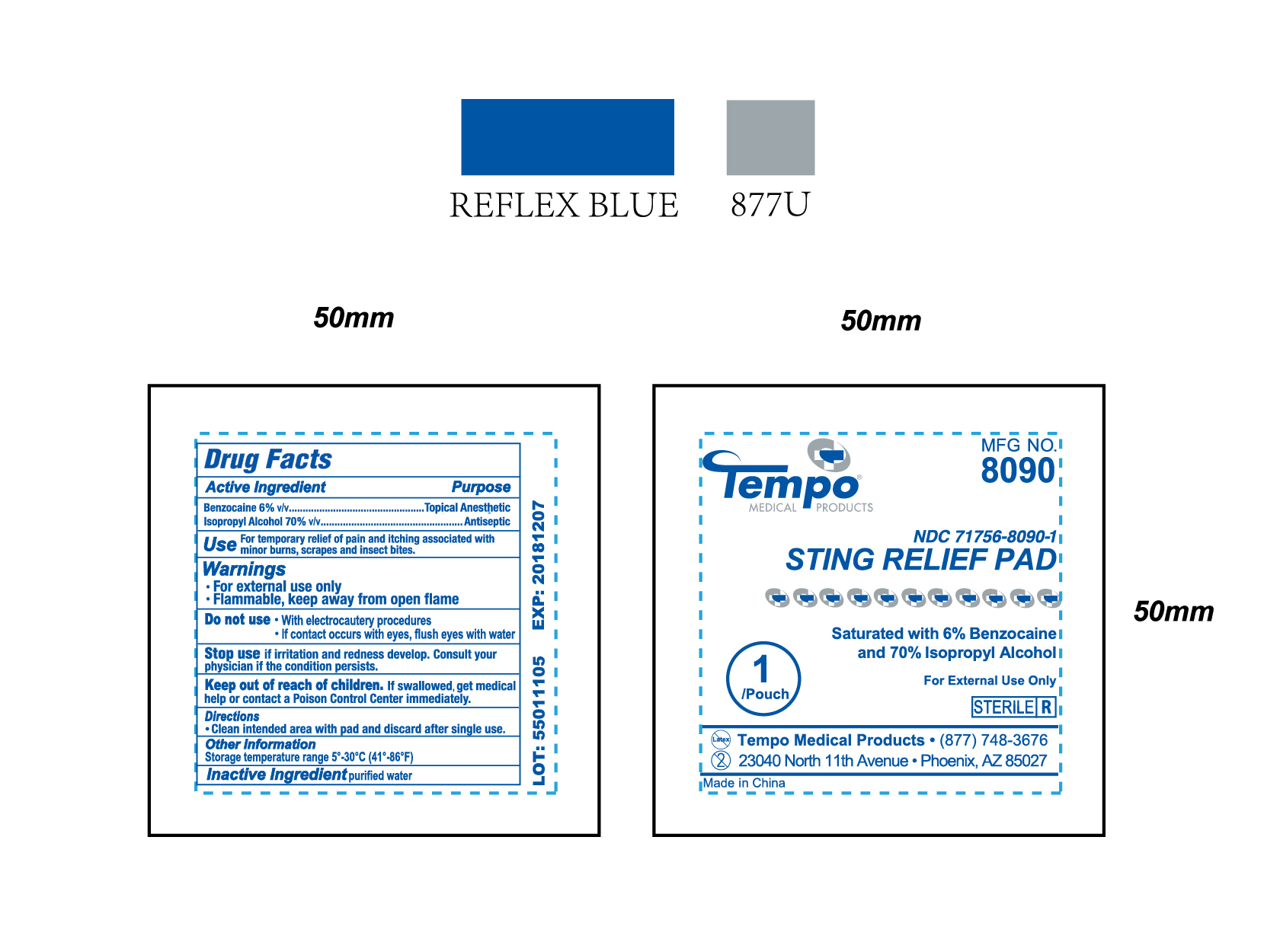 DRUG LABEL: Tempo BZK Towelette
NDC: 71756-8050 | Form: CLOTH
Manufacturer: Tempo Medical Products
Category: otc | Type: HUMAN OTC DRUG LABEL
Date: 20200108

ACTIVE INGREDIENTS: BENZALKONIUM CHLORIDE 0.13 mg/100 mg
INACTIVE INGREDIENTS: CAMPHOR (SYNTHETIC); WATER

Product Label for NDC 71756-8050-1 (BZK Towelette)

Directions

Tear open pouch, unfold and use. Discard after single use.

Warnings

- For external use only
- Flammable, keep away from open flame

Inactive Ingredient

purified water, camphor

Do Not Use / Stop Use / Use

(Do not use)

- On irritated skin or over large areas of the body
- If contact occurs with eyes, flush eyes with water

(Stop use)

if irritation and redness develop. Consult your physician if the condition persists.

(Use)

Cleansing of hands, face and body. Air dries in seconds.

Keep out of reach of children

If swallowed, get medical help or contact a Poison Control Center immediately.

Purpose

Antiseptic Cleanser

Active Ingredient

Benzalkonium Chloride 0.13% v/v

Product Label for NDC 71756-8010-1 (Alcohol Prep Pad)

Directions

Wipe injection site and discard after single use.

Warnings

- For external use only
- Flammable, keep away from open flame

Inactive Ingredient

purified water

Do Not Use / Stop Use / Use

(Do not use)

- With electrocautery procedures
- If contact occurs with eyes, flush eyes with water

(Stop use)

if irritation and redness develop. Consult your physician if the condition persists.

(Use)

For preparation of the skin prior to an injection

Keep out of reach of children

If swallowed, get medical help or contact a Poison Control Center immediately.

Purpose

Antiseptic

Active Ingredient

Isopropyl Alcohol 70% v/v

Product Label for NDC 71756-8090-1 (Sting Relief Pad)

Directions

Clean intended area with pad and discard after single use.

Warnings

- For external use only
- Flammable, keep away from open flame

Inactive Ingredient

purified water

Do Not Use / Stop Use / Use

(Do not use)

- With electrocautery procedures
- If contact occurs with eyes, flush eyes with water

(Stop use)

if irritation and redness develop. Consult your physician if the condition persists.

(Use)

For temporary relief of pain and itching associated with minor burns, scrapes and insect bites.

Keep out of reach of children

If swallowed, get medical help or contact a Poison Control Center immediately.

Purpose

Topical Anesthetic (Benzocaine)

Antiseptic (Isopropyl Alcohol)

Active Ingredient

Benzocaine 6% v/v

Isopropyl Alcohol 70% v/v